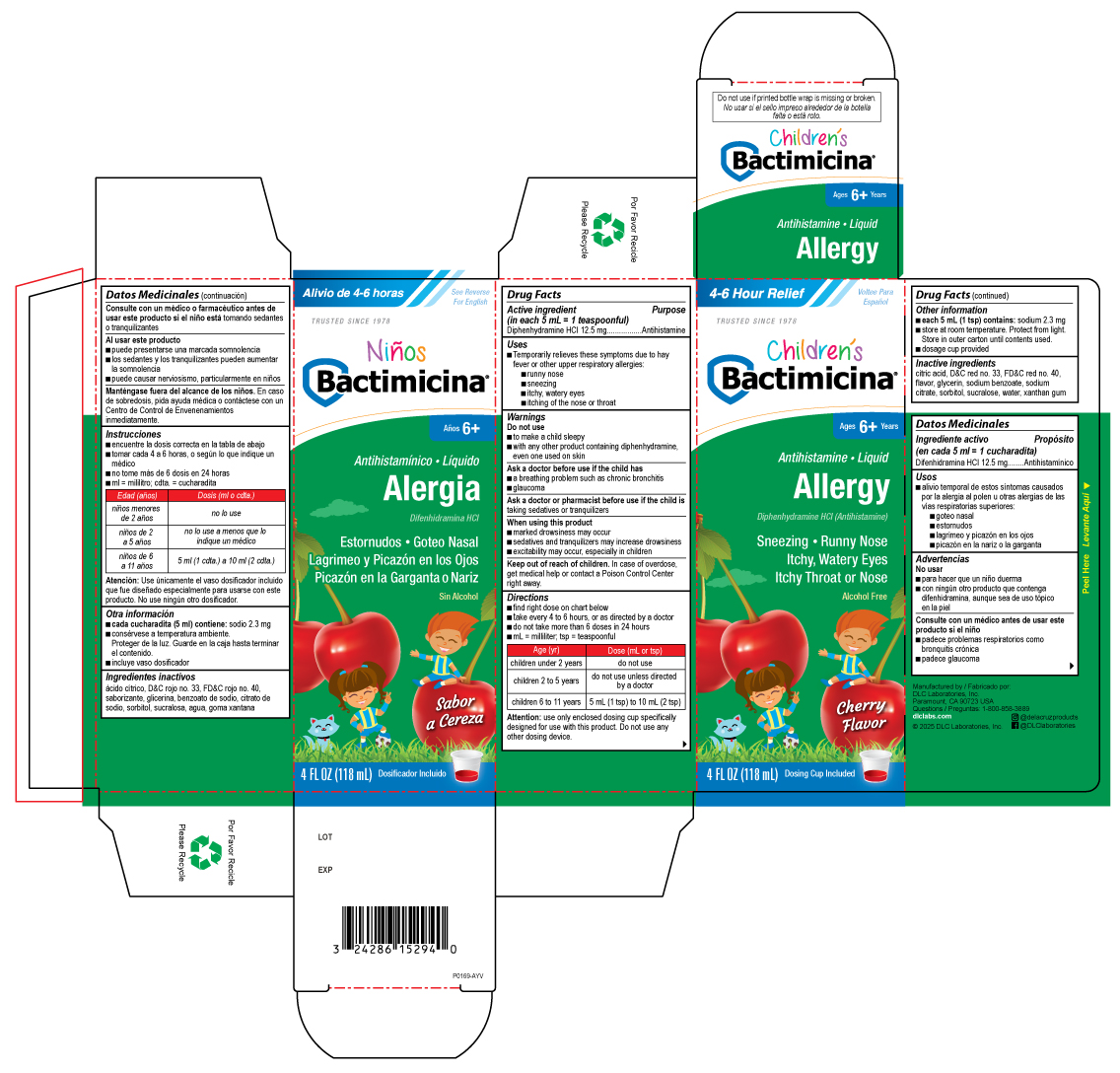 DRUG LABEL: BACTIMICINA CHILDRENS ALLERGY
NDC: 24286-1565 | Form: LIQUID
Manufacturer: DLC Laboratories, Inc.
Category: otc | Type: HUMAN OTC DRUG LABEL
Date: 20250515

ACTIVE INGREDIENTS: DIPHENHYDRAMINE HYDROCHLORIDE 12.5 mg/5 mL
INACTIVE INGREDIENTS: WATER; SUCRALOSE; GLYCERIN; SORBITOL; SODIUM BENZOATE; ANHYDROUS CITRIC ACID; TRISODIUM CITRATE DIHYDRATE; XANTHAN GUM; FD&C RED NO. 40; D&C RED NO. 33

BACTIMICINA® CHILDREN'S ALLERGY

Drug Facts

Active ingredient (in each 5 mL = 1 teaspoonful)

Diphenhydramine HCl 12.5 mg

Purpose

Antihistamine

Uses

- Temporarily relieves these symptoms due to hay fever or other upper respiratory allergies:
  - runny nose
  - sneezing
  - itchy, watery eyes
  - itching of the nose or throat

Warnings

Do not use

- to make a child sleepy
- with any other product containing diphenhydramine, even one used on skin

Ask a doctor before use if the child has

- a breathing problem such as chronic bronchitis
- glaucoma

Ask a doctor or pharmacist before use if the child is taking sedatives or tranquilizers

When using this product

- marked drowsiness may occur
- sedatives and tranquilizers may increase drowsiness
- excitability may occur, especially in children

Keep out of reach of children. In case of overdose, get medical help or contact a Poison Control Center right away.

Directions

- find right dose on chart below
- take every 4 to 6 hours, or as directed by a doctor
- do not take more than 6 doses in 24 hours
- mL = milliliter; tsp = teaspoonful

Age (yr) | Dose (mL or tsp)
children under 2 years | do not use
children 2 to 5 years | do not use unless directed by a doctor
children 6 to 11 years | 5 mL (1 tsp) to 10 mL (2 tsp)

Attention: use only enclosed dosing cup specifically designed for use with this product. Do not use any other dosing device.

Other information

- each 5 mL (1 tsp) contains: sodium 2.3 mg
- store at room temperature. Protect from light. Store in outer carton until contents used.
- dosage cup provided
- do not use if printed bottle wrap is missing or broken

Inactive ingredients

citric acid, D&C red no. 33, FD&C red no. 40, flavor, glycerin, sodium benzoate, sodium citrate, sorbitol, sucralose, water, xanthan gum

Questions

1-800-858-3889

Manufactured by
DLC Laboratories, Inc.
Paramount, CA 90723 USA

PRINCIPAL DISPLAY PANEL - 118 mL Bottle Carton

4-6 Hour Relief

Voltee Para

Español

TRUSTED SINCE 1978

Children's

Bactimicina®

Ages 6+ Years

Antihistamine • Liquid

Allergy

Diphenhydramine HCL (Antihistamine)

Sneezing • Runny Nose

Itchy, Watery Eyes

Itchy Throat or Nose

Alcohol Free

Cherry Flavor

4 FL OZ (118 mL) Dosing Cup Included